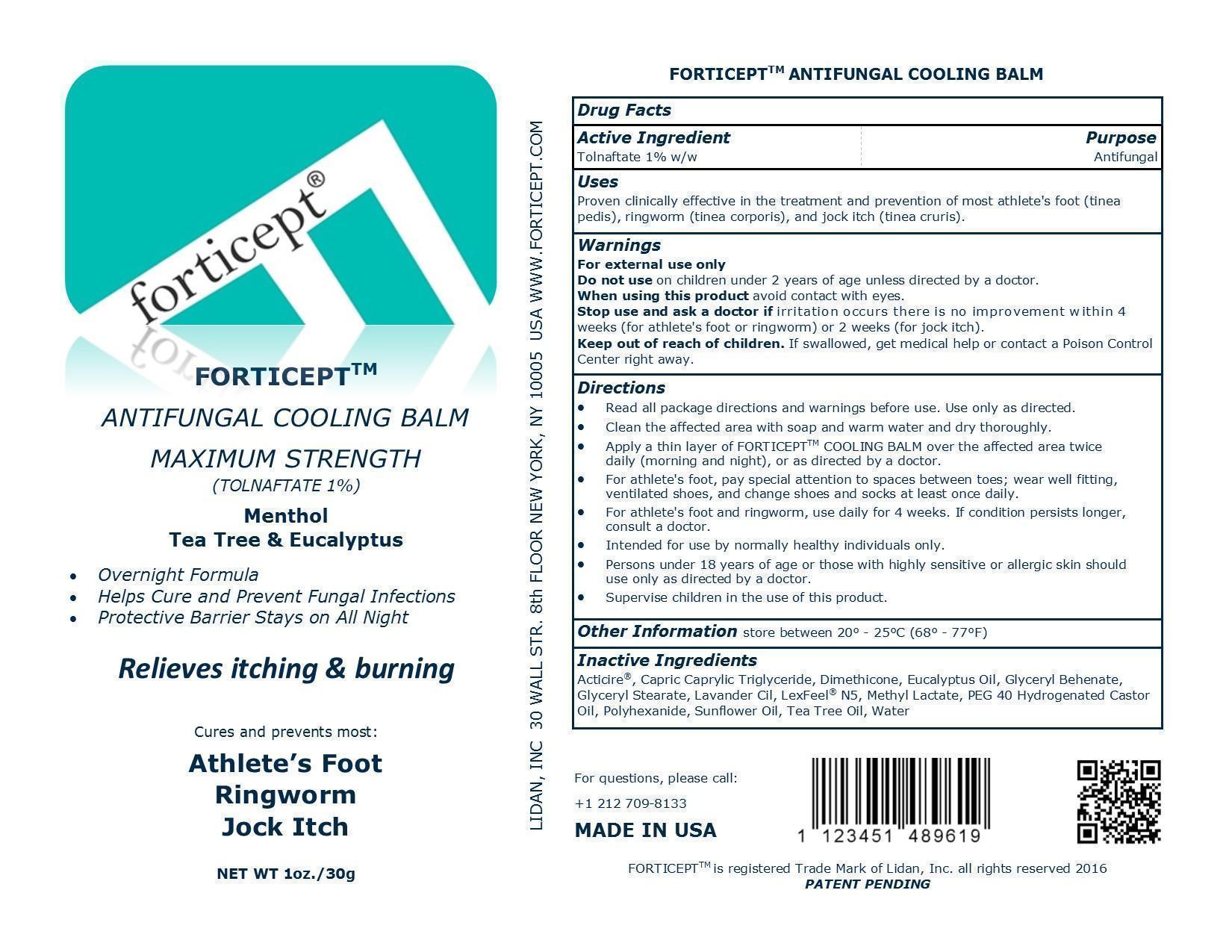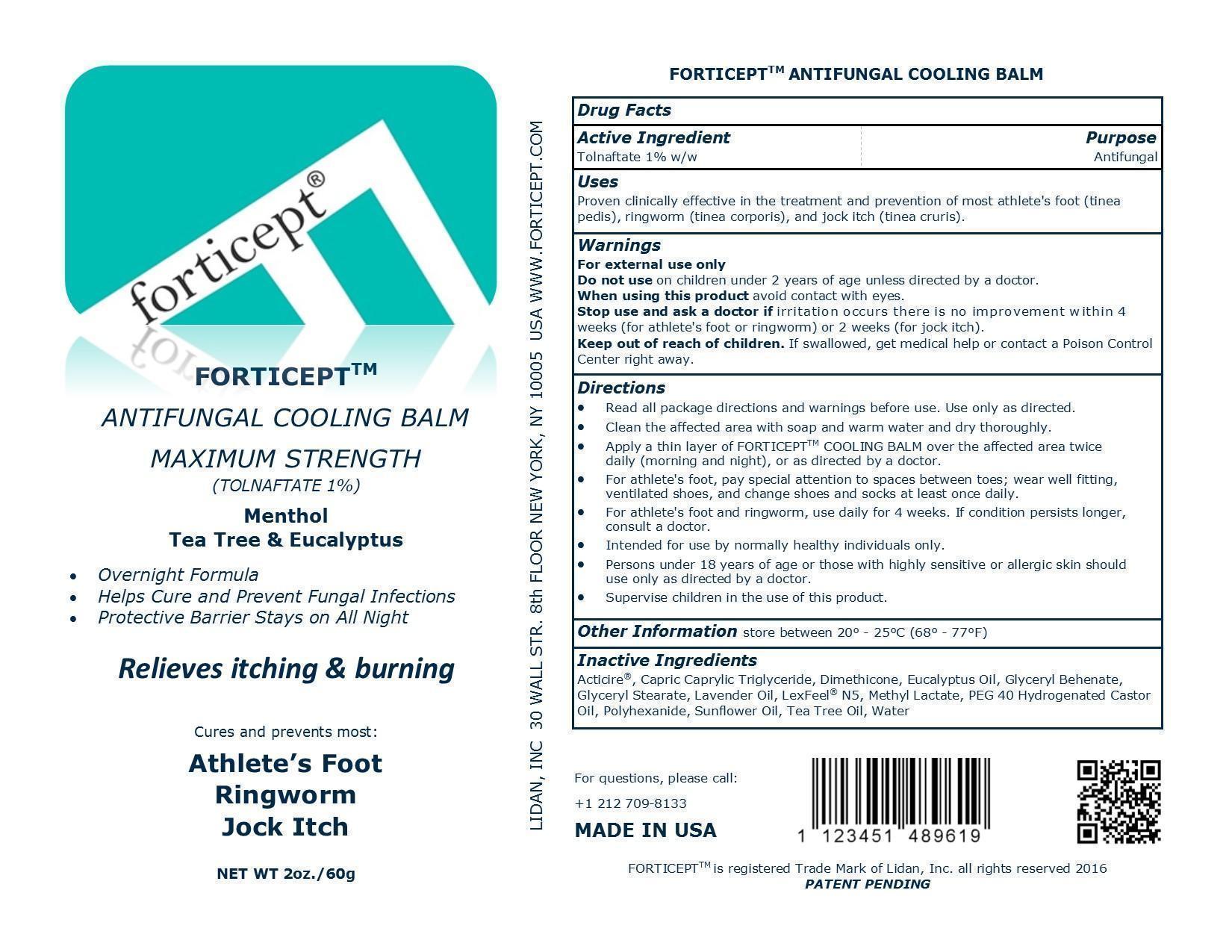 DRUG LABEL: Forticept Antifungal Balm
NDC: 52261-0100 | Form: liquid
Manufacturer: Cosco International, Inc.
Category: otc | Type: HUMAN OTC DRUG LABEL
Date: 20160511

ACTIVE INGREDIENTS: tolnaftate 10 g/1000 g
INACTIVE INGREDIENTS: water 415.7 g/1000 g; sunflower oil 158.225 g/1000 g; dimethicone 150 g/1000 g; DIHEPTYL SUCCINATE 80 g/1000 g; glyceryl monostearate 65 g/1000 g; GLYCERYL DIBEHENATE 50 g/1000 g; peg-40 castor oil 25 g/1000 g; polyglyceryl-10 oleate 24.675 g/1000 g; POLIHEXANIDE HYDROCHLORIDE 10 g/1000 g; methyl lactate, (-)- 4 g/1000 g; tea tree oil 2.5 g/1000 g; eucalyptus oil 1.8 g/1000 g; GLYCERYL CAPRATE 1.05 g/1000 g; ACACIA DECURRENS FLOWER 1.05 g/1000 g

Drug Facts

Active Ingredient/Purpose

Tolnaftate 1% w/w........................Antifungal

Uses

Proven clinically effective in the treatment and prevention of most athlete's foot (tinea pedis), ringworm (tinea corporis), and jock itch (tinea cruris).

Warnings

For external use only

Do not use on children under 2 years of age unless direceted by a doctor.

When using this product avoid contact with eyes.

Stop use and ask a doctor if irritation occurs or there is no improvement within 4 weeks (for athlete's foot or ringworm) or 2 weeks (for jock itch).

Keep out of reach of children. If swallowed, get medical help or contact a Poison Control Center right away.

Directions

- Read all package directions and warnings before use. Use only as directed.
- Clean the affected area with soap and warm water and dry thoroughly.
- Apply a thin layer of FORTICEPTTM COOLING BALM over the affected area twice daily (morning and night), or as directed by a doctor.
- For athlete's foot, pay special attention to spaces between toes; wear well fitting, ventilated shoes, and change shoes and socks at least once daily.
- For athlete's foot and ringworm, use daily for 4 weeks. If condition persists longer, consult a doctor.
- Intended for use by normally healthy individuals only.
- Persons under 18 years of age or those with highly sensitive or allergic skin should use only as directed by a doctor.
- Supervise children in the use of this product.

Other Information store between 20° - 25°C (68° - 77°F)

Inactive ingredients:

Acticire®, Capric Caprylic Triglyceride, Dimethicone, Eucalyptus Oil, Glyceryl Behenate, Glyceryl Stearate, Lavender Oil, LexFeel® N5, Methyl Lactate, PEG 40 Hydrogenated Castor Oil, Polyhexanide, Sunflower Oil, Tea Tree Oil, Water